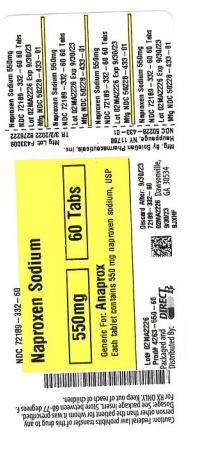 DRUG LABEL: Naproxen Sodium
NDC: 72189-332 | Form: TABLET
Manufacturer: Direct Rx
Category: prescription | Type: HUMAN PRESCRIPTION DRUG LABEL
Date: 20250121

ACTIVE INGREDIENTS: NAPROXEN SODIUM 550 mg/1 1
INACTIVE INGREDIENTS: CELLULOSE, MICROCRYSTALLINE; MAGNESIUM STEARATE; POLYETHYLENE GLYCOL 400; POVIDONE, UNSPECIFIED; TALC; TITANIUM DIOXIDE; HYPROMELLOSE, UNSPECIFIED

Naproxen Sodium

Medication Guide for Nonsteroidal Anti-inflammatory Drugs (NSAIDs)
This Medication Guide has been approved by the U.S. Food and Drug Administration.
Revised: 5/2021

What is the most important information I should know about medicines called Nonsteroidal Anti-inflammatory Drugs (NSAIDs)?

NSAIDs can cause serious side effects, including:

Increased risk of a heart attack or stroke that can lead to death. This risk may happen early in treatment and may increase:

with increasing doses of NSAIDs
with longer use of NSAIDs

Do not take NSAIDs right before or after a heart surgery called a “coronary artery bypass graft (CABG)."
Avoid taking NSAIDs after a recent heart attack, unless your healthcare provider tells you to. You may have an increased risk of another heart attack if you take NSAIDs after a recent heart attack.

Increased risk of bleeding, ulcers, and tears (perforation) of the esophagus (tube leading from the mouth to the stomach), stomach and intestines:

anytime during use
without warning symptoms
that may cause death

The risk of getting an ulcer or bleeding increases with:

past history of stomach ulcers, or stomach or intestinal bleeding with use of NSAIDs
taking medicines called “corticosteroids”, “anticoagulants”, “SSRIs”, or “SNRIs”

increasing doses of NSAIDs
longer use of NSAIDs
smoking
drinking alcohol

older age
poor health
advanced liver disease
bleeding problems

NSAIDs should only be used:

exactly as prescribed
at the lowest dose possible for your treatment
for the shortest time needed

What are NSAIDs?

NSAIDs are used to treat pain and redness, swelling, and heat (inflammation) from medical conditions such as different types of arthritis, menstrual cramps, and other types of short-term pain.

Who should not take NSAIDs?

Do not take NSAIDs:

if you have had an asthma attack, hives, or other allergic reaction with aspirin or any other NSAIDs.
right before or after heart bypass surgery.

Before taking NSAIDs, tell your healthcare provider about all of your medical conditions, including if you:

have liver or kidney problems
have high blood pressure
have asthma
are pregnant or plan to become pregnant. Taking NSAIDs at about 20 weeks of pregnancy or later may harm your unborn baby. If you need to take NSAIDs for more than 2 days when you are between 20 and 30 weeks of pregnancy, your healthcare provider may need to monitor the amount of fluid in your womb around your baby. You should not take NSAIDs after about 30 weeks of pregnancy.
are breastfeeding or plan to breast feed.

Tell your healthcare provider about all of the medicines you take, including prescription or over-the-counter medicines, vitamins or herbal supplements. NSAIDs and some other medicines can interact with each other and cause serious side effects. Do not start taking any new medicine without talking to your healthcare provider first.

What are the possible side effects of NSAIDs?
NSAIDs can cause serious side effects, including:
See “What is the most important information I should know about medicines called Nonsteroidal Anti-inflammatory Drugs (NSAIDs)?”

new or worse high blood pressure
heart failure
liver problems including liver failure
kidney problems including kidney failure
low red blood cells (anemia)
life-threatening skin reactions
life-threatening allergic reactions

Other side effects of NSAIDs include: stomach pain, constipation, diarrhea, gas, heartburn, nausea, vomiting, and dizziness. Get emergency help right away if you get any of the following symptoms:

• shortness of breath or trouble breathing

• slurred speech

• chest pain

• swelling of the face or throat

• weakness in one part or side of your body

Stop taking your NSAID and call your healthcare provider right away if you get any of the following symptoms:

nausea
more tired or weaker than usual
diarrhea
itching
your skin or eyes look yellow
indigestion or stomach pain
flu-like symptoms

vomit blood
there is blood in your bowel movement or it is black and sticky like tar
unusual weight gain
skin rash or blisters with fever
swelling of the arms, legs, hands and feet

If you take too much of your NSAID, call your healthcare provider or get medical help right away.

These are not all the possible side effects of NSAIDs. For more information, ask your healthcare provider or pharmacist about NSAIDs. Call your doctor for medical advice about side effects. You may report side effects to FDA at 1-800-FDA-1088.

Other information about NSAIDs

Aspirin is an NSAID but it does not increase the chance of a heart attack. Aspirin can cause bleeding in the brain, stomach, and intestines. Aspirin can also cause ulcers in the stomach and intestines.
Some NSAIDs are sold in lower doses without a prescription (over-the counter). Talk to your healthcare provider before using over-the-counter NSAIDs for more than 10 days.

General information about the safe and effective use of NSAIDs

Medicines are sometimes prescribed for purposes other than those listed in a Medication Guide. Do not use NSAIDs for a condition for which it was not prescribed. Do not give NSAIDs to other people, even if they have the same symptoms that you have. It may harm them.

If you would like more information about NSAIDs, talk with your healthcare provider. You can ask your pharmacist or healthcare provider for information about NSAIDs that is written for health professionals.

Manufactured by: ScieGen Pharmaceuticals Inc, Hauppauge, NY 11788, USA

For more information, call 1-855-724-3436

HOW SUPPLIED

Naproxen Sodium Tablets USP, 275 mg are white, capsule-shaped, film coated tablets debossed with “432” on one side and “SG” on other side.

Bottles of 30 NDC 50228-432-30
Bottles of 100 NDC 50228-432-01
Bottles of 500 NDC 50228-432-05
Bottles of 1,000 NDC 50228-432-10

Naproxen Sodium Tablets USP, 550 mg are white, capsule-shaped, film coated tablets, debossed with “433” on one side and “S & G” on either side of functional scoreline on the other side.

Bottles of 30 NDC 50228-433-30
Bottles of 100 NDC 50228-433-01
Bottles of 500 NDC 50228-433-05
Bottles of 1,000 NDC 50228-433-10

Store at 15° to 30°C (59° to 86°F) in well-closed containers.

CLINICAL STUDIES

Naproxen has been studied in patients with rheumatoid arthritis, osteoarthritis, polyarticular juvenile idiopathic arthritis, ankylosing spondylitis, tendonitis and bursitis, and acute gout. Improvement in patients treated for rheumatoid arthritis was demonstrated by a reduction in joint swelling, a reduction in duration of morning stiffness, a reduction in disease activity as assessed by both the investigator and patient, and by increased mobility as demonstrated by a reduction in walking time. Generally, response to naproxen has not been found to be dependent on age, sex, severity or duration of rheumatoid arthritis.

In patients with osteoarthritis, the therapeutic action of naproxen has been shown by a reduction in joint pain or tenderness, an increase in range of motion in knee joints, increased mobility as demonstrated by a reduction in walking time, and improvement in capacity to perform activities of daily living impaired by the disease.

In a clinical trial comparing standard formulations of naproxen 375 mg twice a day (750 mg a day) vs 750 mg twice a day (1500 mg/day), 9 patients in the 750 mg group terminated prematurely because of adverse events. Nineteen patients in the 1500 mg group terminated prematurely because of adverse events. Most of these adverse events were gastrointestinal events.

In clinical studies in patients with rheumatoid arthritis, osteoarthritis, and polyarticular juvenile idiopathic arthritis, naproxen has been shown to be comparable to aspirin and indomethacin in controlling the aforementioned measures of disease activity, but the frequency and severity of the milder gastrointestinal adverse effects (nausea, dyspepsia, heartburn) and nervous system adverse effects (tinnitus, dizziness, lightheadedness) were less in naproxen-treated patients than in those treated with aspirin or indomethacin.

In patients with ankylosing spondylitis, naproxen has been shown to decrease night pain, morning stiffness and pain at rest. In double-blind studies the drug was shown to be as effective as aspirin, but with fewer side effects.

In patients with acute gout, a favorable response to naproxen was shown by significant clearing of inflammatory changes (e.g., decrease in swelling, heat) within 24 to 48 hours, as well as by relief of pain and tenderness.

Naproxen has been studied in patients with mild to moderate pain secondary to postoperative, orthopedic, postpartum episiotomy and uterine contraction pain and dysmenorrhea. Onset of pain relief can begin within 1 hour in patients taking naproxen and within 30 minutes in patients taking naproxen sodium. Analgesic effect was shown by such measures as reduction of pain intensity scores, increase in pain relief scores, decrease in numbers of patients requiring additional analgesic medication, and delay in time to remedication. The analgesic effect has been found to last for up to 12 hours.

Naproxen may be used safely in combination with gold salts and/or corticosteroids; however, in controlled clinical trials, when added to the regimen of patients receiving corticosteroids, it did not appear to cause greater improvement over that seen with corticosteroids alone. Whether naproxen has a “steroid-sparing” effect has not been adequately studied. When added to the regimen of patients receiving gold salts, naproxen did result in greater improvement. Its use in combination with salicylates is not recommended because there is evidence that aspirin increases the rate of excretion of naproxen and data are inadequate to demonstrate that naproxen and aspirin produce greater improvement over that achieved with aspirin alone. In addition, as with other NSAIDs, the combination may result in higher frequency of adverse events than demonstrated for either product alone.

In 51Cr blood loss and gastroscopy studies with normal volunteers, daily administration of 1100 mg of naproxen sodium has been demonstrated to cause statistically significantly less gastric bleeding and erosion than 3250 mg of aspirin.

DESCRIPTION

Naproxen sodium tablets, USP are nonsteroidal anti-inflammatory drugs and available as white capsule-shape tablets, containing 275 mg or 550 mg of naproxen sodium for oral administration.

Naproxen sodium is a member of the arylacetic acid group of nonsteroidal anti-inflammatory drugs. The chemical name for naproxen sodium is (S)-6-methoxy-α-methyl-2-naphthaleneacetic acid, sodium salt. Naproxen sodium has a molecular weight of 252.25 and a molecular formula of C 14H 13NaO 3. It has the following structural formula:

[Structural Formula]

Naproxen is white to creamy crystalline powder. It is soluble in water and methanol, practically insoluble in chloroform, toluene and acetone, sparingly soluble in alcohol.

Each naproxen sodium tablet, USP contains the following inactive ingredients: hypromellose, magnesium stearate, microcrystalline cellulose, polyethylene glycol 400, povidone, talc, and titanium dioxide.

OVERDOSAGE

Symptoms following acute NSAID overdosages have been typically limited to lethargy, drowsiness, nausea, vomiting, and epigastric pain, which have been generally reversible with supportive care. Gastrointestinal bleeding has occurred. Hypertension, acute renal failure, respiratory depression, and coma have occurred, but were rare [ see Warnings and Precautions (5.1, 5.2) ].Because naproxen sodium may be rapidly absorbed, high and early blood levels should be anticipated.

A few patients have experienced convulsions, but it is not clear whether or not these were drug-related. It is not known what dose of the drug would be life threatening. [ see Warnings and Precautions (5.1, 5.2, 5.4, 5.6)].

Manage patients with symptomatic and supportive care following an NSAID overdosage. There are no specific antidotes. Consider emesis and/or activated charcoal (60 to 100 grams in adults, 1 to 2 grams per kg of body weight in pediatric patients) and/or osmotic cathartic in symptomatic patients seen within four hours of ingestion or in patients with a large overdosage (5 to 10 times the recommended dosage). Forced diuresis, alkalinization of urine, hemodialysis, or hemoperfusion may not be useful due to high protein binding.

For additional information about overdosage treatment contact a poison control center (1-800-222-1222).

INDICATIONS AND USAGE

Naproxen sodium tablets are non-steroidal anti-inflammatory drugs indicated for:
the relief of the signs and symptoms of:

rheumatoid arthritis
osteoarthritis
ankylosing spondylitis
polyarticular juvenile idiopathic arthritis

Naproxen sodium tablets are also indicated for:
the relief of the signs and symptoms of:

tendonitis
bursitis
acute gout

the management of:

pain
primary dysmenorrhea

DOSAGE AND ADMINISTRATION

2.1 General Dosing Instructions

Carefully consider the potential benefits and risks of naproxen sodium tablets and other treatment options before deciding to use naproxen sodium tablets. Use the lowest effective dose for the shortest duration consistent with individual patient treatment goals [ see WARNINGS AND PRECAUTIONS (5)].

After observing the response to initial therapy with naproxen sodium tablets, the dose and frequency should be adjusted to suit an individual patient’s needs.

Naproxen-containing products such as naproxen sodium tablets, and other naproxen products should not be used concomitantly since they all circulate in the plasma as the naproxen anion.

2.2 Rheumatoid Arthritis, Osteoarthritis and Ankylosing Spondylitis

The recommended dosages of naproxen sodium tablets are shown in Table 1.

Table 1: Recommended dosages for naproxen sodium tablets

Naproxen sodium tablets 275 mg (naproxen 250 mg with 25 mg sodium)
550 mg (naproxen 500 mg with 50 mg sodium) twice daily

During long-term administration, the dose of naproxen may be adjusted up or down depending on the clinical response of the patient. A lower daily dose may suffice for long-term administration.

The morning and evening doses do not have to be equal in size and the administration of the drug more frequently than twice daily is not necessary.

The morning and evening doses do not have to be equal in size and administration of the drug more frequently than twice daily does not generally make a difference in response.

In patients who tolerate lower doses well, the dose may be increased to naproxen 1500 mg/day for limited periods of up to 6 months when a higher level of anti-inflammatory/analgesic activity is required. When treating such patients with naproxen 1500 mg/day, the physician should observe sufficient increased clinical benefits to offset the potential increased risk.

2.3 Polyarticular Juvenile Idiopathic Arthritis

Naproxen solid-oral dosage forms may not allow for the flexible dose titration needed in pediatric patients with polyarticular juvenile idiopathic arthritis. A liquid formulation may be more appropriate for weight-based dosing and due to the need for dose flexibility in children.

In pediatric patients, doses of 5 mg/kg/day produced plasma levels of naproxen similar to those seen in adults taking 500 mg of naproxen [ see CLINICAL PHARMACOLOGY (12)]. The recommended total daily dose of naproxen is approximately 10 mg/kg given in 2 divided doses. Dosing with naproxen tablets is not appropriate for children weighing less than 50 kilograms.

2.4 Management of Pain, Primary Dysmenorrhea, and Acute Tendonitis and Bursitis

The recommended starting dose of naproxen sodium tablets is 550 mg followed by 550 mg every 12 hours or 275 mg every 6 to 8 hours as required. The initial total daily dose should not exceed 1375 mg of naproxen sodium. Thereafter, the total daily dose should not exceed 1100 mg of naproxen sodium. Because the sodium salt of naproxen is more rapidly absorbed, naproxen sodium tablets are recommended for the management of acute painful conditions when prompt onset of pain relief is desired.

2.5 Acute Gout

Naproxen sodium tablets may also be used at a starting dose of 825 mg followed by 275 mg every 8 hours.

2.6 Non-Interchangeability with Other Formulations of Naproxen

Different dose strengths and formulations (e.g., tablets, suspension) of naproxen are not interchangeable. This difference should be taken into consideration when changing strengths or formulations.